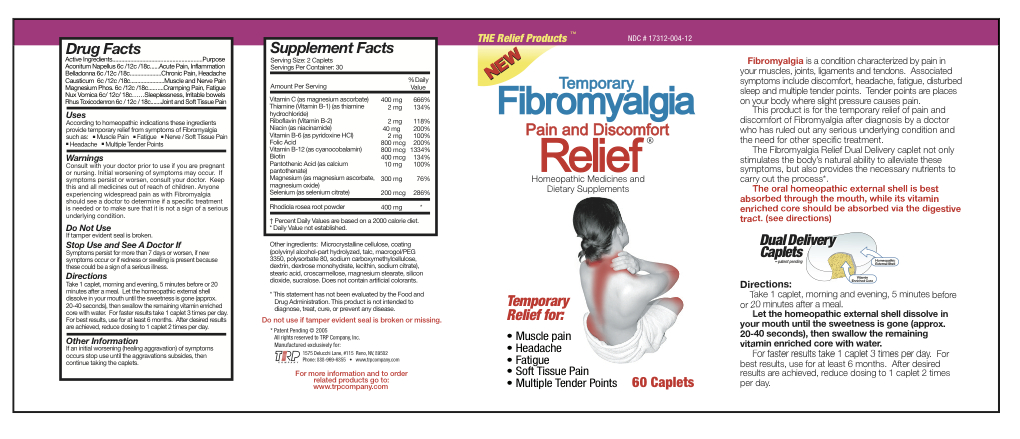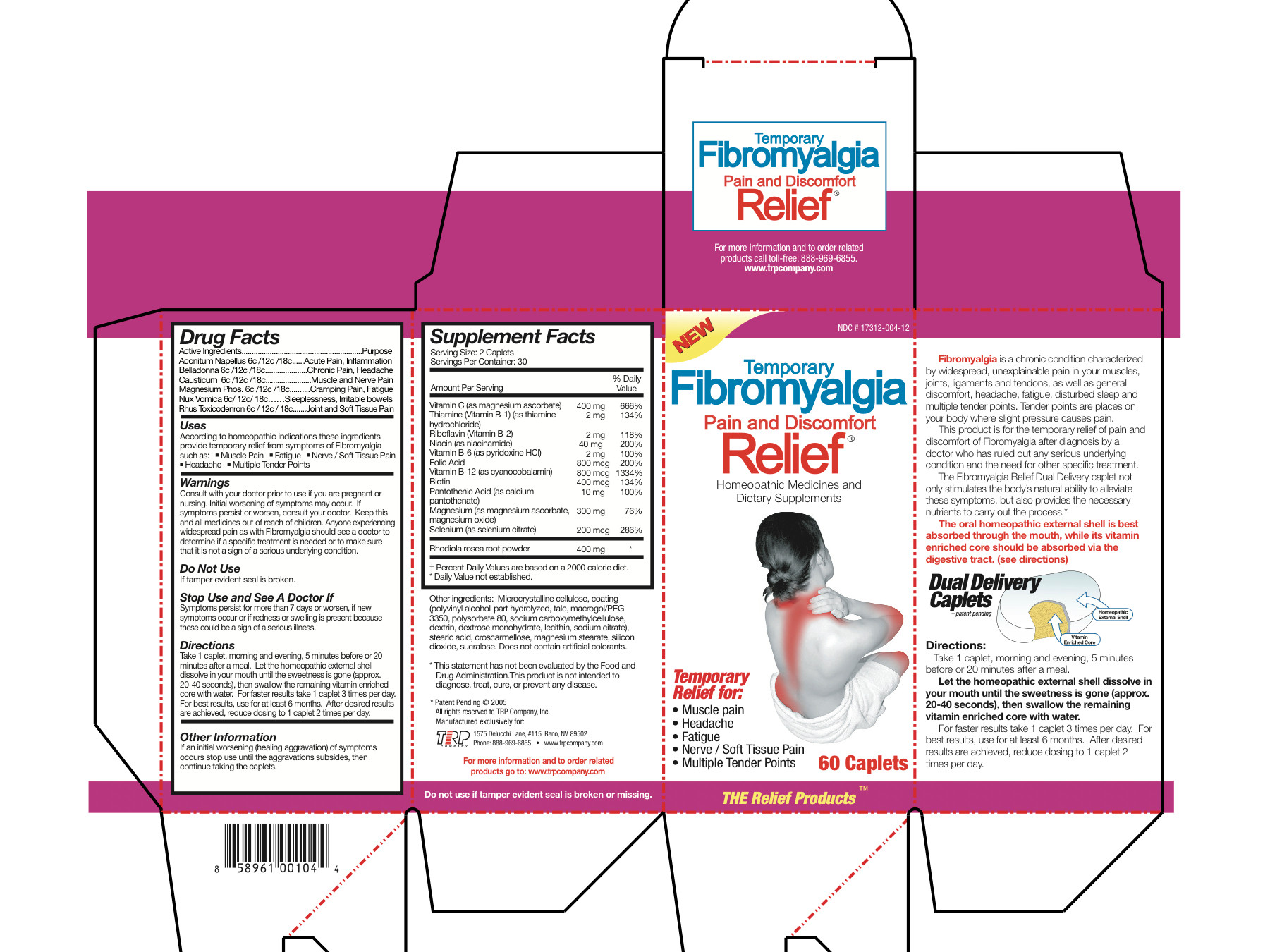 DRUG LABEL: Temporary Fibromyalgia Pain and Discomfort Relief
NDC: 17312-004 | Form: Tablet, Multilayer
Manufacturer: TRP Company
Category: homeopathic | Type: HUMAN OTC DRUG LABEL
Date: 20120531

ACTIVE INGREDIENTS: Aconitum Napellus 6 [hp_C]/1 1; Atropa Belladonna 6 [hp_C]/1 1; Causticum 6 [hp_C]/1 1; Magnesium Phosphate, Dibasic Trihydrate 6 [hp_C]/1 1; Strychnos Nux-Vomica Seed 6 [hp_C]/1 1; Toxicodendron Pubescens Leaf 6 [hp_C]/1 1; Magnesium Ascorbate 200 mg/1 1; Thiamine Hydrochloride 1 mg/1 1; Riboflavin 1 mg/1 1; Niacinamide 20 mg/1 1; Pyridoxine Hydrochloride 1 mg/1 1; Folic Acid 400 ug/1 1; Cyanocobalamin 400 ug/1 1; Biotin 200 ug/1 1; Calcium Pantothenate 5 mg/1 1; Magnesium Ascorbate 75 mg/1 1; Magnesium Oxide 75 mg/1 1; Selenium 100 ug/1 1; Sedum Roseum Root 200 mg/1 1
INACTIVE INGREDIENTS: Cellulose, Microcrystalline; Polyvinyl Alcohol; Talc; Polyethylene Glycol 3350; Polysorbate 80; Carboxymethylcellulose Sodium; Icodextrin; Dextrose Monohydrate; Egg Phospholipids; Sodium Citrate; Stearic Acid; Croscarmellose; Magnesium Stearate; Silicon Dioxide; Sucralose

Temporary Fibromyalgia Pain and Discomfort Relief

Homeopathic Purpose

Aconitum Napellus | 6c/12c/18c | Acute Pain, Inflammation
Belladonna | 6c/12c/18c | Chronic Pain, Headache
Causticum | 6c/12c/18c | Muscle and Nerve Pain
Magnesium Phos | 6c/12c/18c | Cramping Pain, Fatigue
Nux Vomica | 6c/12c/18c | Sleeplessness, Irritable bowels
Rhus Toxicodendron | 6c/12c/18c | Joint and Soft Tissue Pain

Active Ingredients

Aconitum Napellus | 6c/12c/18c
Belladonna | 6c/12c/18c
Causticum | 6c/12c/18c
Magnesium Phos | 6c/12c/18c
Nux Vomica | 6c/12c/18c
Rhus Toxicodendron | 6c/12c/18c
Magnesium Ascorbate | 200 mg
Thiamine Hydrochloride | 1 mg
Riboflavin | 1 mg
Niacinamide | 20 mg
Pyridoxine Hydrochloride | 1 mg
Folic Acid | 400 mcg
Cyanocobalamin | 400 mcg
Biotin | 200 mcg
Calcium Pantothenate | 5 mg
Magnesium Ascorbate | 75 mg
Magnesium Oxide | 75 mg
Selenium | 100 mcg
Sedum Roseum Root | 200 mg

Inactive Ingredients

Microcrystalline cellulose

Polyvinyl Alcohol

Talc

Macrogol/PEG 3350

Polysorbate 80

Sodium Carboxymethylcellulose

Dextrin

Dextrose Monohydrate

Lecithin

Sodium Citrate

Stearic Acid

Croscarmellose

Magnesium Stearate

Silicon Dioxide

Sucralose

Uses

According to homeopathic indications these ingredients provide temporary relief from symptoms of Fibromyalgia such as:
- Muscle Pain
- Fatigue
- Nerve/Soft Tissue Pain
- Headache
- Multiple Tender Points

Warnings

- Consult with your doctor prior to use if you are pregnant or nursing.
- Initial worsening of symptoms may occur.
- If symptoms persist or worsen, consult your doctor.
- Anyone experiencing widespread pain as with Fibromyalgia should see a doctor to determine if a specific treatment is needed or to make sure that it is not a sign of a serious underlying condition.

KEEP OUT OF REACH OF CHILDREN

Keep this and all medicines out of reach of children.

Do not use

If tamper evident seal is broken.

Stop Use and See A Doctor If

If Symptoms persist for more than 7 days or worsen or if new symptoms occur or if redness or swelling is present because these could be a sign of a serious illness.

Directions

Take 1 caplet, morning and evening, 5 minutes before or 20 minutes after a meal. Let the homeopathic external shell dissolve in your mouth until the sweetness is gone (approx. 20-40 seconds), then swallow the remaining vitamin enriched core with water. For faster results take 1 caplet 3 times per day. For best results, use for at least 6 months. After desired results are achieved, reduce dosing to 1 caplet 2 times per day.

Other Information

If an initial worsening (healing aggravation) of symptoms occurs stop use until the aggravations subsides, then continue taking the caplets.

QUESTIONS

TRP Company
1575 Delucchi Lane #115
Reno, NV 89502
888-969-6855
www.trpcompany.com